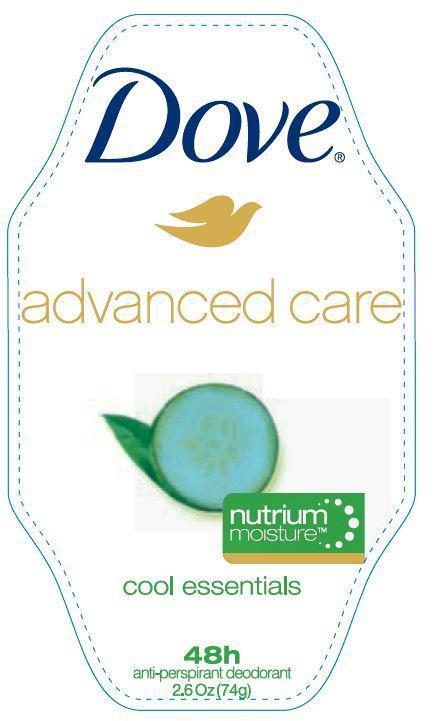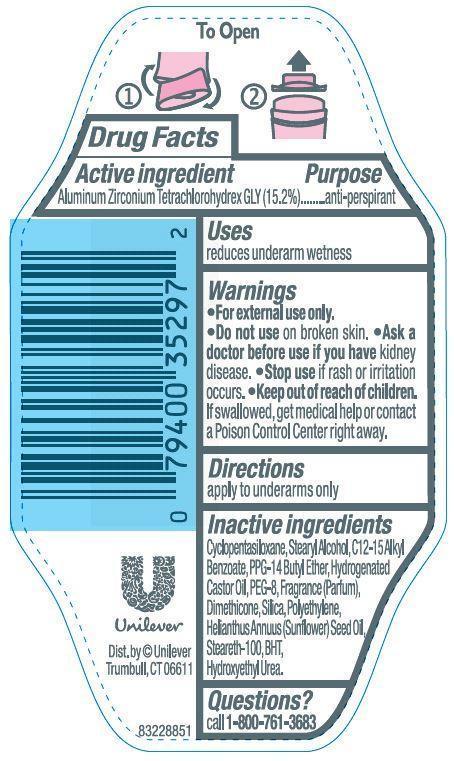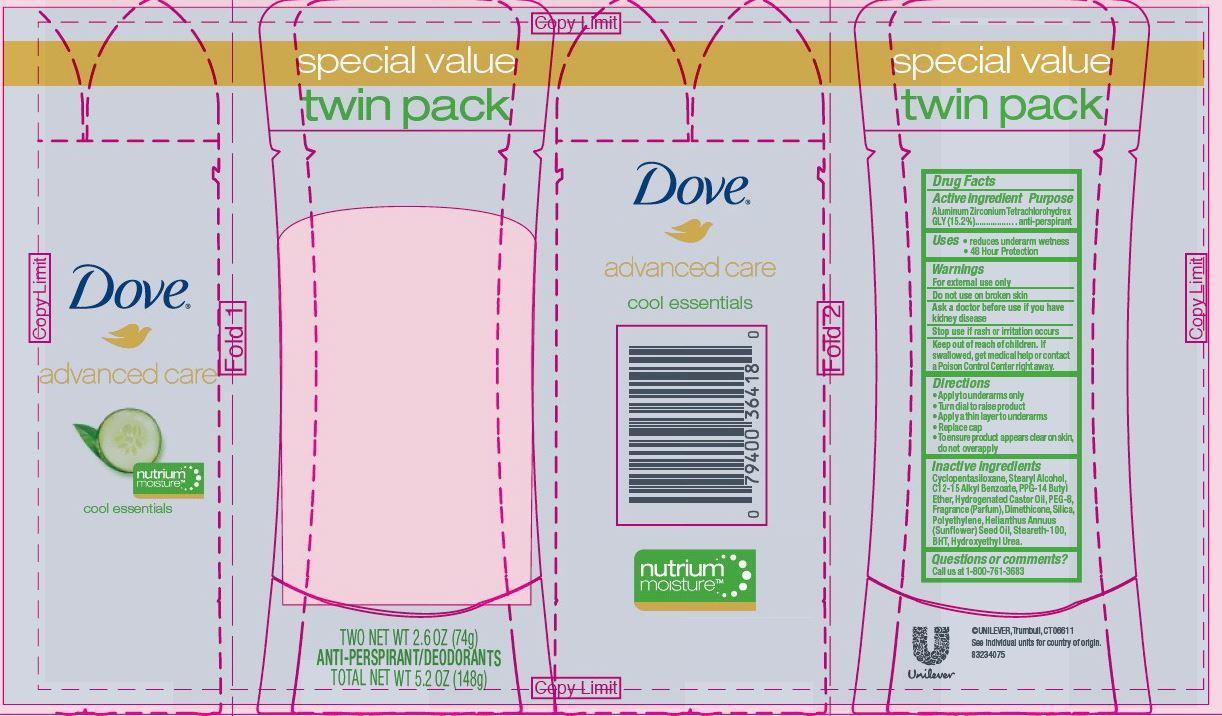 DRUG LABEL: Dove
NDC: 64942-1343 | Form: STICK
Manufacturer: Conopco Inc. d/b/a Unilever
Category: otc | Type: HUMAN OTC DRUG LABEL
Date: 20241106

ACTIVE INGREDIENTS: ALUMINUM ZIRCONIUM TETRACHLOROHYDREX GLY 15.2 g/100 g
INACTIVE INGREDIENTS: CYCLOMETHICONE 5; PPG-14 BUTYL ETHER; STEARYL ALCOHOL; HYDROGENATED CASTOR OIL; DIMETHICONE; BUTYLATED HYDROXYTOLUENE; STEARETH-100; SUNFLOWER OIL; ALKYL (C12-15) BENZOATE; HIGH DENSITY POLYETHYLENE; POLYETHYLENE GLYCOL 400; SILICON DIOXIDE; HYDROXYETHYL UREA

Dove Advanced Care Cool Essentials Antiperspirant deodorant

Active Ingredient

Aluminum Zirconium Tetrachlorohydrex GLY (15.2%)

Purpose
anti-perspirant

Uses

reduces underarm wetness

Warnings
· For External Use Only.

· Do not use on broken skin.

· Ask a doctor before use if you have kidney disease.

· Stop use if rash or irritation occurs.

· Keep out of reach of children. If swallowed, get medical help or contact a Poison Control Center right away.

Directions
apply to underarms only

Inactive ingredients
Cyclopentasiloxane, Stearyl Alcohol, C12-15 Alkyl Benzoate, PPG-14 Butyl Ether, Hydrogenated Castor Oil, PEG-8, Fragrance (Parfum), Dimethicone, Silica, Polyethylene, Helianthus Annuus (Sunflower) Seed Oil, Steareth-100, BHT, Hydroxyethyl Urea.

Questions? Call toll-free 1-800-761-3683